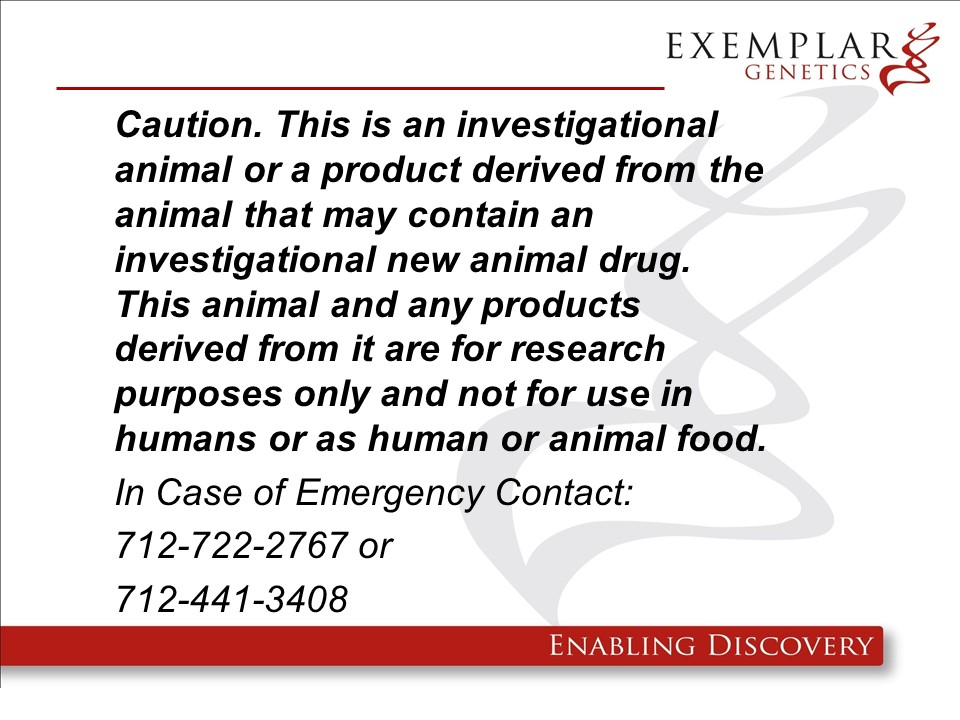 DRUG LABEL: ExeGen PKD miniswine
NDC: 86093-2002 | Form: NOT APPLICABLE
Manufacturer: Exemplar Genetics, Llc
Category: other | Type: INTENTIONAL ANIMAL GENOMIC ALTERATION LABEL
Date: 20250617

ACTIVE INGREDIENTS: PKD1 +/R3278C-BLAST RDNA CONSTRUCT AT EXON 29 IN YUCATAN MINIATURE SWINE 1 [arb'U]/1 [arb'U]

pPKD-Blast in miniswine

ExeGen PKD miniswine are genetically engineered yucatan miniature swine containing the rDNA construct pPKD-Blast which exhibit similar phenotypes to human patients with PKD. These pigs are intended to be used as large animal models of the human disease. We will not be requesting a food use authorization and the carcasses and all materials generated from these animals will be destroyed by incineration.

Product Definition: A specific line of Yucatan miniature pigs (Sus scrofa domesticus), including heterozygous offspring resulting from a heterozygous founder, in which the PKD1 gene has been disrupted by the homologous recombination of a single copy of a mutated PKD1-PGK construct resulting in a point mutation for use in biomedical research. The desirable animal will be a heterozygote PKD1 +/R3277C Blast miniswine.

Warning: This product is from a genetically engineered animal and may contain an investigational new animal drug. It is for research purposes only and not for use in humans or as food/feed unless authorization has been granted by the US Food and Drug Administration. In case of emergency or release contact Exemplar Genetics at 712-722-2767 or 712-441-3408.